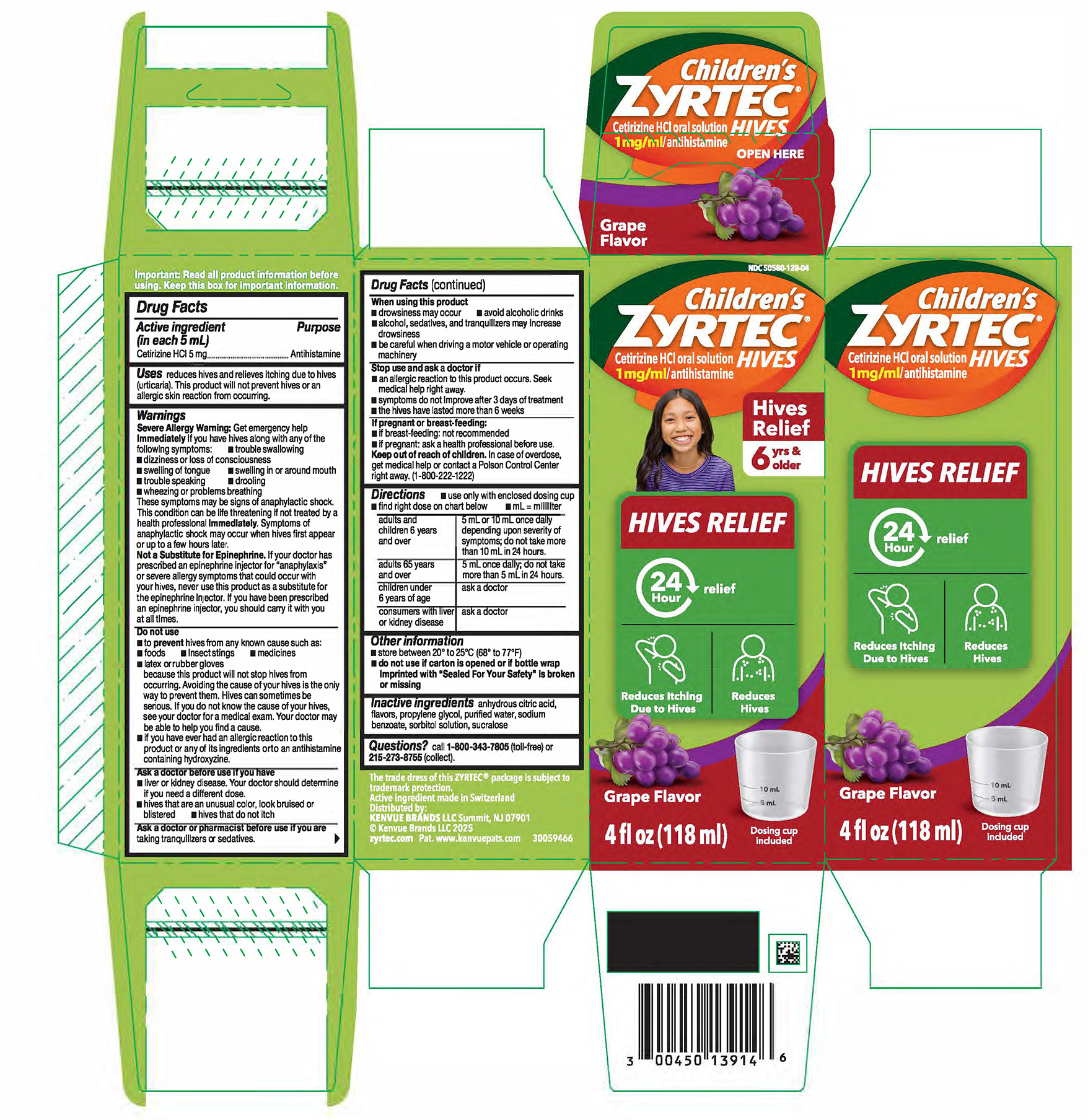 DRUG LABEL: ZYRTEC HIVES
NDC: 50580-128 | Form: SOLUTION
Manufacturer: Kenvue Brands LLC
Category: otc | Type: HUMAN OTC DRUG LABEL
Date: 20250616

ACTIVE INGREDIENTS: CETIRIZINE HYDROCHLORIDE 1 mg/1 mL
INACTIVE INGREDIENTS: SUCRALOSE; ANHYDROUS CITRIC ACID; PROPYLENE GLYCOL; SODIUM BENZOATE; SORBITOL SOLUTION; WATER

ZYRTEC Hives

Drug Facts

Active ingredient (in each 5 mL)

Cetirizine HCI 5 mg

Purpose

Antihistamine

Uses

reduces hives and relieves itching due to hives (urticaria). This product will not prevent hives or an allergic skin reaction from occurring.

Warnings

Severe Allergy Warning: Get emergency help immediately if you have hives along with any of the
following symptoms:
■ trouble swallowing
■ dizziness or loss of consciousness
■ swelling of tongue
■ swelling in or around mouth
■ trouble speaking
■ drooling
■ wheezing or problems breathing
These symptoms may be signs of anaphylactic shock.
This condition can be life threatening if not treated by a health professional immediately. Symptoms of anaphylactic shock may occur when hives first appear or up to a few hours later.
Not a Substitute for Epinephrine. If your doctor has prescribed an epinephrine injector for anaphylaxis or severe allergy symptoms that could occur with your hives, never use this product as a substitute for the epinephrine injector. If you have been prescribed an epinephrine injector, you should carry it with you at all times.

Do not use

■ to prevent hives from any known cause such as:
■ foods
■ insect stings
■ medicines
■ latex or rubber gloves
because this product will not stop hives from occurring. Avoiding the cause of your hives is the only
way to prevent them. Hives can sometimes be serious. If you do not know the cause of your hives,
see your doctor for a medical exam. Your doctor may be able to help you find a cause.
■ if you have ever had an allergic reaction to this product or any of its ingredients or to an antihistamine containing hydroxyzine.

Ask a doctor before use if you have
■ liver or kidney disease. Your doctor should determine if you need a different dose.
■ hives that are an unusual color, look bruised or blistered
■ hives that do not itch

Ask a doctor or pharmacist before use if you are taking tranquilizers or sedatives.

When using this product
■ drowsiness may occur
■ avoid alcoholic drinks
■ alcohol, sedatives, and tranquilizers may increase drowsiness
■ be careful when driving a motor vehicle or operating machinery

Stop use and ask a doctor if
■ an allergic reaction to this product occurs. Seek medical help right away.
■ symptoms do not improve after 3 days of treatment
■ the hives have lasted more than 6 weeks

If pregnant or breast-feeding:
■ if breast-feeding: not recommended
■ if pregnant: ask a health professional before use.

Keep out of reach of children. In case of overdose, get medical help or contact a Poison Control Center
right away. (1-800-222-1222)

Directions

■ use only with enclosed dosing cup
■ find right dose on chart below
■ mL = milliliter

adults and children 6 years and over | 5 mL or 10 mL once daily depending upon severity of symptoms; do not take more than 10 mL in 24 hours.
adults 65 years and over | 5 mL once daily; do not take more than 5 mL in 24 hours.
children under 6 years of age | ask a doctor
consumers with liver or kidney disease | ask a doctor

Other information
■ store between 20° to 25°C (68° to 77°F)

■ do not use if carton is opened or if bottle wrap imprinted with “Sealed For Your Safety” is broken or missing

Inactive ingredients

Inactive ingredients anhydrous citric acid, flavors, propylene glycol, purified water, sodium benzoate,
sorbitol solution, sucralose

Questions?

Questions? call 1-800-343-7805 (toll-free) or 215-273-8755 (collect)

PRINCIPAL DISPLAY PANEL

NDC 50580-128-04

Children’s

ZYRTEC® HIVES

Cetirizine HCl oral solution
1 mg/ml/antihistamine

Hives Relief

6 yrs & old

HIVES RELIEF

24 Hour relief

Reduces Itching Due to Hives

Reduces Hives

Grape Flavor

4 fl oz (118ml)

Dosing cup included